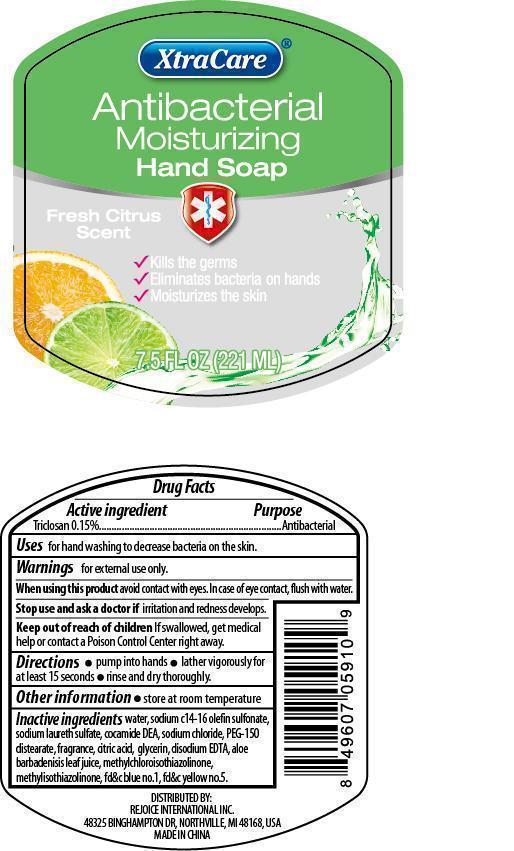 DRUG LABEL: XtraCare Antibacterial Hand Cleanse
NDC: 57337-069 | Form: SOAP
Manufacturer: Rejoice International, Inc.
Category: otc | Type: HUMAN OTC DRUG LABEL
Date: 20250212

ACTIVE INGREDIENTS: TRICLOSAN 3.3 mg/221 mL
INACTIVE INGREDIENTS: WATER; SODIUM C14-16 OLEFIN SULFONATE; SODIUM LAURETH SULFATE; COCO DIETHANOLAMIDE; SODIUM CHLORIDE; PEG-150 DISTEARATE; CITRIC ACID MONOHYDRATE; GLYCERIN; EDETATE DISODIUM; ALOE VERA LEAF; METHYLCHLOROISOTHIAZOLINONE; METHYLISOTHIAZOLINONE; FD&C BLUE NO. 1; FD&C YELLOW NO. 5

XtraCare Antibacterial Hand Cleanse

Active Ingredient Purpose

Triclosan 0.15%...................................Antibacterial

PURPOSE

Antibacterial Moisturizing Hand Soap

Fresh Citrus Scent

- Kills the germs
- Eliminates bacteria on hands
- Moisturizes the skin

Keep out of reach of children. If swallowed, get medical help or contact a Poison Control Center right away.

Uses

for handwashing to decrease bacteria on the skin.

Warnings

When using this product avoid contact with eyes. In case of eye contact, flush with water.

Stop use and ask a doctor if irritation and redness develops.

Directions

- pump into hands
- lather vigorously for at least 15 seconds
- rinse and dry thoroughly.

Inactive Ingredientsi

water, sodium c14-16 olefin sulfonate, sodium laureth sulfate, cocamide DEA, sodium chloride, PEG-150 distearate, fragrance, citric acid, glycerin, disodium EDTA, aloe barbadensis leaf juice, methylchloroisothiazolinone, methylisothiazolinone, fd&c blue no. 1, fd&c yellow no. 5.

Other information

- store at room temperature

DISTRIBUTED BY:

REJOICE INTERNATIONAL, INC.

48325 BINGHAMPTON DR., NORTHVILLE, MI 48168, USA

MADE IN CHINA